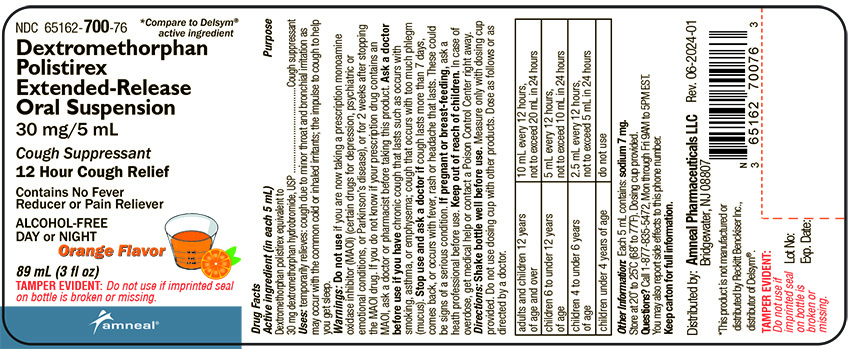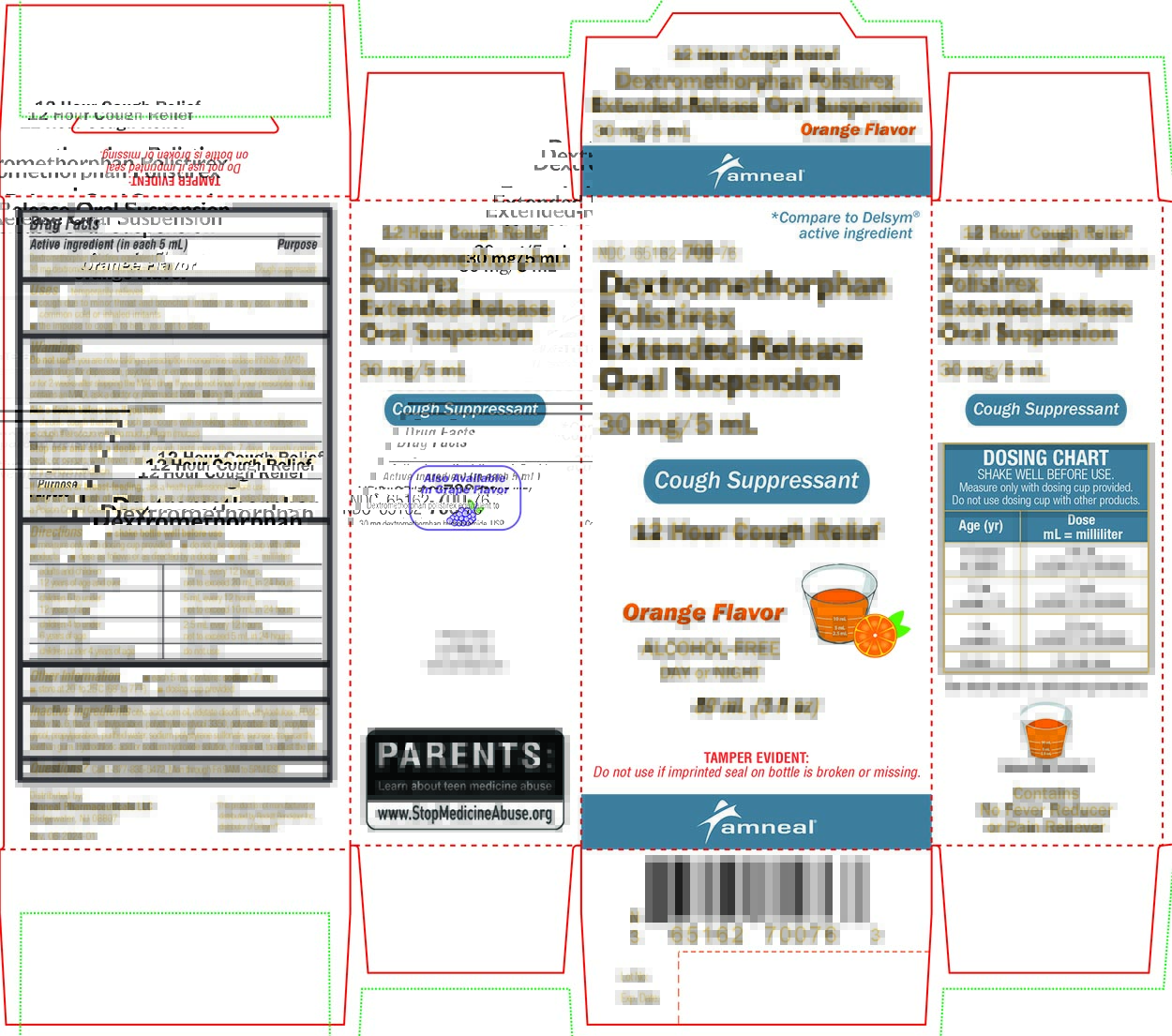 DRUG LABEL: Dextromethorphan Polistirex Extended-Release
NDC: 65162-700 | Form: SUSPENSION
Manufacturer: Amneal Pharmaceuticals LLC
Category: otc | Type: HUMAN OTC DRUG LABEL
Date: 20240627

ACTIVE INGREDIENTS: DEXTROMETHORPHAN HYDROBROMIDE 30 mg/5 mL
INACTIVE INGREDIENTS: CITRIC ACID MONOHYDRATE; CORN OIL; EDETATE DISODIUM; ETHYLCELLULOSES; FD&C YELLOW NO. 6; METHYLPARABEN; POLYETHYLENE GLYCOL 3350; POLYSORBATE 80; PROPYLENE GLYCOL; PROPYLPARABEN; WATER; SUCROSE; TRAGACANTH; XANTHAN GUM; HYDROCHLORIC ACID; SODIUM HYDROXIDE; SODIUM POLYSTYRENE SULFONATE

Dextromethorphan Polistirex Extended-Release Suspension
12 Hour Cough Relief
Orange

Drug Facts

OTC - ACTIVE INGREDIENT

Active ingredient (in each 5 mL)

Dextromethorphan polistirex equivalent to 30 mg dextromethorphan hydrobromide, USP

OTC - PURPOSE

Purpose

Cough suppressant

INDICATIONS AND USAGE

Uses

Temporarily relieves

- cough due to minor throat and bronchial irritation as may occur with the common cold or inhaled irritants
- the impulse to cough to help you get to sleep

WARNINGS

OTC - DO NOT USE

Do not use if you are now taking a prescription monoamine oxidase inhibitor (MAOI) (certain drugs for depression, psychiatric or emotional conditions, or Parkinson's disease), or for 2 weeks after stopping the MAOI drug. If you do not know if your prescription drug contains an MAOI, ask a doctor or pharmacist before taking this product.

OTC - ASK DOCTOR

Ask a doctor before use if you have

- chronic cough that lasts such as occurs with smoking, asthma or emphysema
- cough that occurs with too much phlegm (mucus)

Stop use and ask a doctor if cough lasts more than 7 days, cough comes back, or occurs with fever, rash or headache that lasts. These could be signs of a serious condition.

OTC - PREGNANCY OR BREAST FEEDING

If pregnant or breast-feeding, ask a health professional before use.

OTC - KEEP OUT OF REACH OF CHILDREN

Keep out of reach of children. In case of overdose, get medical help or contact a Poison Control Center right away.

DOSAGE AND ADMINISTRATION

Directions

- shake bottle well before use
- measure only with dosing cup provided
- do not use dosing cup with other products
- dose as follows or as directed by a doctor
- mL = milliliter

adults and children 12 years of age and over | 10 mL every 12 hours, not to exceed 20 mL in 24 hours
children 6 to under 12 years of age | 5 mL every 12 hours, not to exceed 10 mL in 24 hours
children 4 to under 6 years of age | 2.5 mL every 12 hours, not to exceed 5 mL in 24 hours
children under 4 years of age | do not use

Other information

- each 5 mL contains: sodium 7 mg
- store at 20° to 25°C (68° to 77°F)
- dosing cup provided

INACTIVE INGREDIENT

Inactive ingredients

citric acid, corn oil, edetate disodium, ethylcellulose, FD&C Yellow No. 6, flavor, methylparaben, polyethylene glycol 3350, polysorbate 80, propylene glycol, propylparaben, purified water, sodium polystyrene sulfonate, sucrose, tragacanth, xanthan gum.

Hydrochloric acid or sodium hydroxide solution, if required, to adjust the pH.

OTC - QUESTIONS

Questions?

Call 1-877-835-5472, Mon through Fri 9AM to 5PM EST.

Distributed by:
Amneal Pharmaceuticals LLC
Bridgewater, NJ 08807

Rev. 06-2024-01